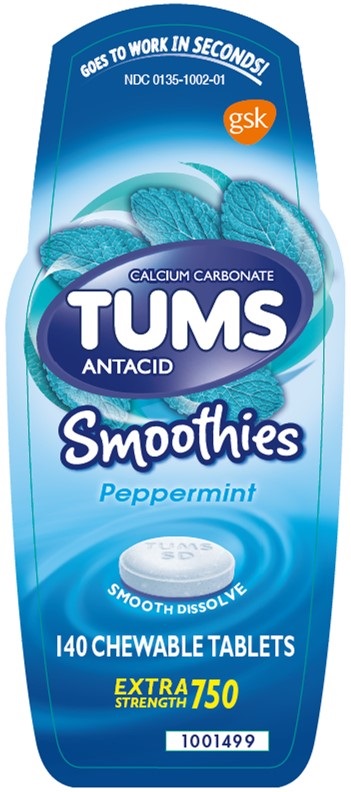 DRUG LABEL: TUMS
NDC: 0135-1002 | Form: TABLET, CHEWABLE
Manufacturer: Haleon US Holdings LLC
Category: otc | Type: HUMAN OTC DRUG LABEL
Date: 20240314

ACTIVE INGREDIENTS: CALCIUM CARBONATE 750 mg/1 1
INACTIVE INGREDIENTS: STARCH, CORN; DEXTROSE, UNSPECIFIED FORM; MAGNESIUM STEARATE; MALTODEXTRIN; MICROCRYSTALLINE CELLULOSE; SORBITOL; SUCROSE; TALC

Drug Facts

Active ingredient (per tablet)

Calcium Carbonate 750 mg

Purpose

Antacid

Uses

relieves

- heartburn
- acid indigestion
- sour stomach
- upset stomach associated with these symptoms

Warnings

Ask a doctor or pharmacist before use if you are

presently taking a prescription drug. Antacids may interact with certain prescription drugs.

When using this product

- do not take more than 10 tablets in 24 hours
- if pregnant do not take more than 6 tablets in 24 hours
- do not use the maximum dosage for more than 2 weeks except under the advice and supervision of a doctor

Directions

- adults and children 12 years of age and over: chew 2-4 tablets as symptoms occur, or as directed by a doctor. Chew or crush tablets completely before swallowing.
- do not take for symptoms that persist for more than 2 weeks unless advised by a doctor

Other information

- each tablet contains: elemental calcium 300 mg, magnesium 10 mg
- store below 30oC (86oF). Keep the container tightly closed.

Inactive ingredients

corn starch, dextrose, flavor, magnesium stearate, maltodextrin, microcrystalline cellulose, sorbitol, sucrose, talc

Questions?

1-800-897-7535

Additional information

DO NOT USE IF PRINTED SEAL UNDER CAP IS TORN OR MISSING.

©2021 GSK group of companies or its licensor.

Dist. By:

GSK Consumer Healthcare

Warren, NJ 07059

Principal Display Panel

NDC 0135-1002-01

TUMS

CALCIUM CARBONATE

ANTACID

GOES TO WORK IN SECONDS!

Smoothies

Peppermint

SMOOTH DISSOLVE

140 CHEWABLE TABLETS

1001499 Front Label

1001500 Back Label